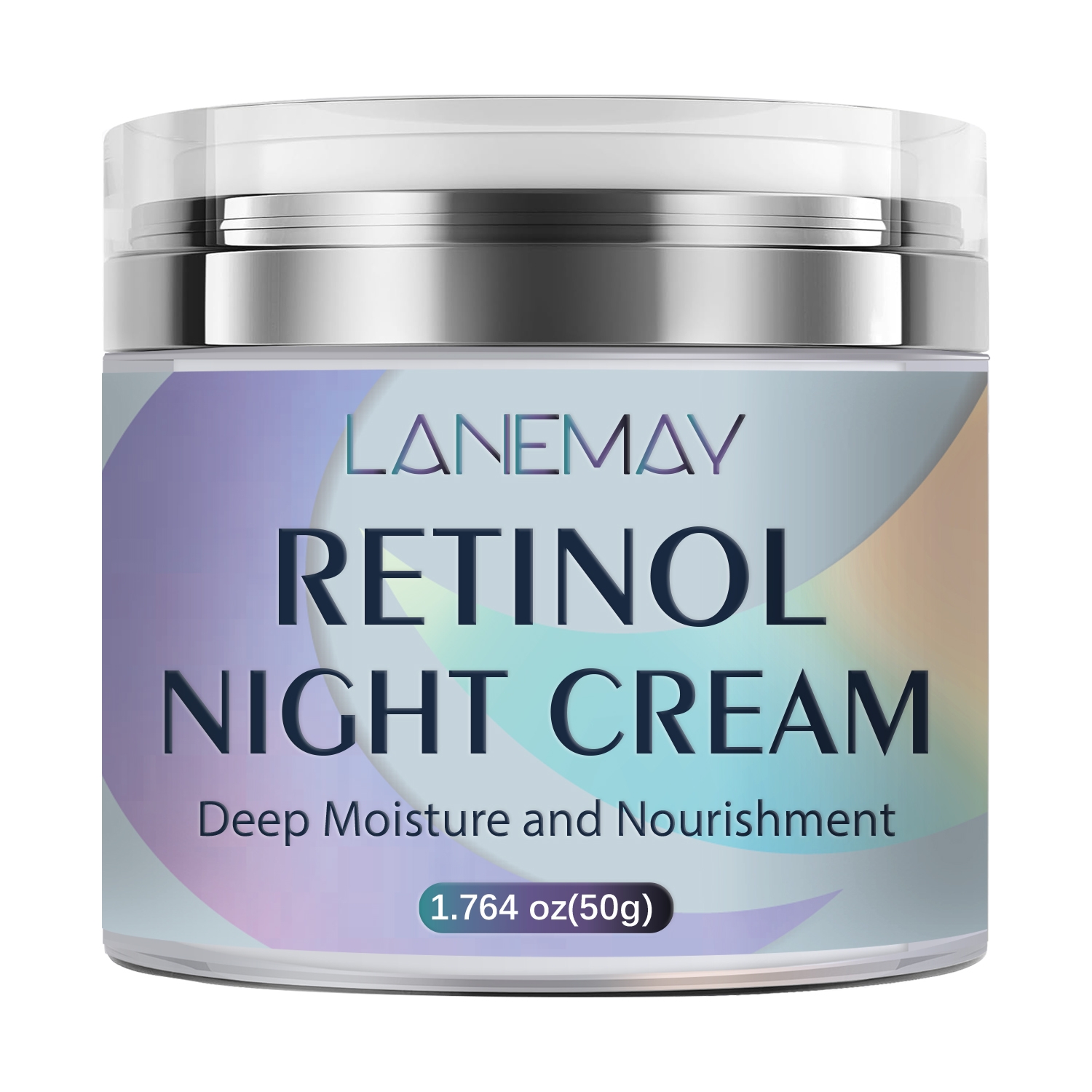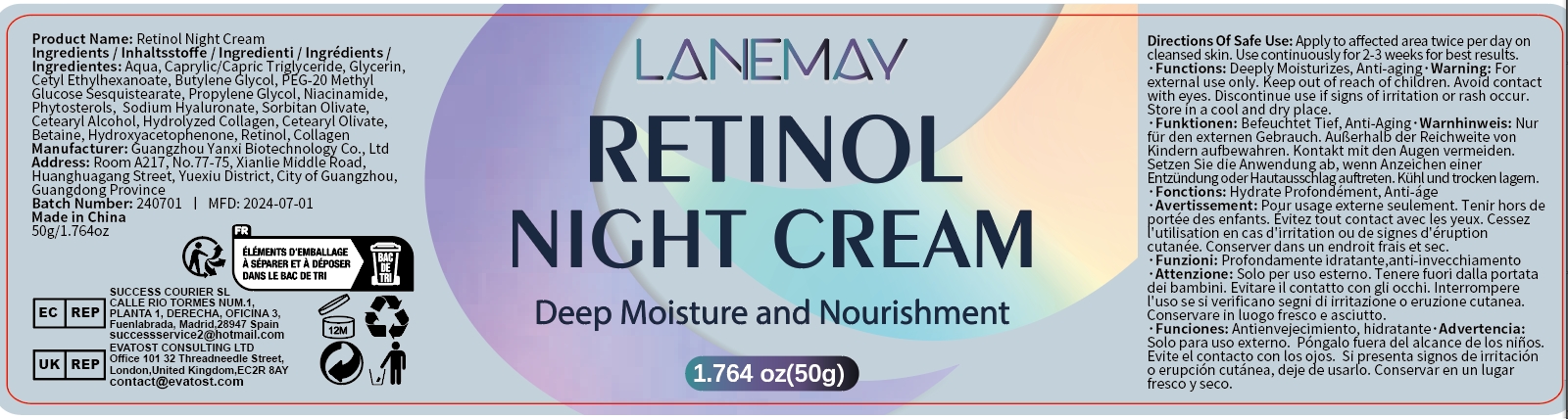 DRUG LABEL: Retinol Night Cream
NDC: 84025-184 | Form: CREAM
Manufacturer: Guangzhou Yanxi Biotechnology Co.. Ltd
Category: otc | Type: HUMAN OTC DRUG LABEL
Date: 20240909

ACTIVE INGREDIENTS: GLYCERIN 5 mg/50 g; CETYL ETHYLHEXANOATE 3 mg/50 g
INACTIVE INGREDIENTS: WATER

DOSAGE AND ADMINISTRATION

Cream for moisturizing wet facial skin

WARNINGS

keep out of children

INACTIVE INGREDIENT

AQUA

INDICATIONS AND USAGE

For daily skin care

keep out of children

PURPOSE

Haves moisturizing effect, deeply moisturizes the skin